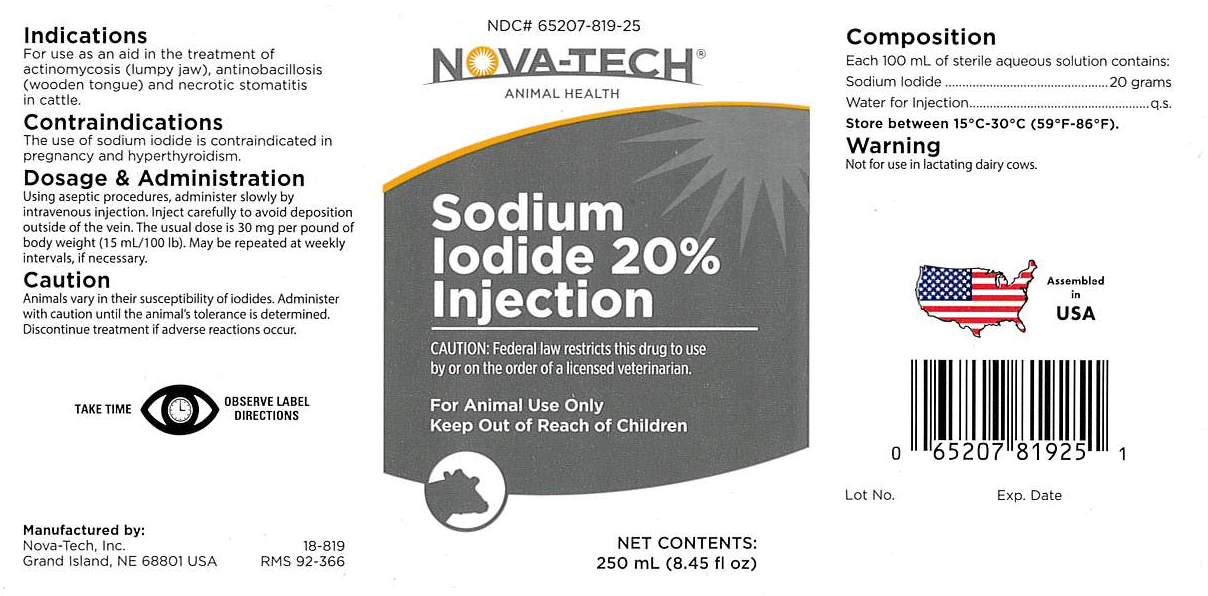 DRUG LABEL: Sodium Iodide
NDC: 65207-819 | Form: INJECTION, SOLUTION
Manufacturer: Nova-Tech, Inc.
Category: animal | Type: PRESCRIPTION ANIMAL DRUG LABEL
Date: 20190822

ACTIVE INGREDIENTS: SODIUM IODIDE 20 g/100 mL

SODIUM IODIDE 20%

INDICATIONS

For use as an aid in the treatment of actinomycosis (lumpy jaw), actinobacillosis (wooden tongue) and necrotic stomatitis in cattle.

CONTRAINDICATIONS

The use of sodium iodide is contraindicated in pregnancy and hyperthyroidism.

CAUTION

Animals vary in their susceptibility of iodides. Administer with caution until the animal's tolerance is determined. Discontinue treatment if adverse reactions occur.

DOSAGE AND ADMINISTRATION:

Using aspetic procedures, administer slowly
by intravenous injection. Inject carefully to
avoid deposition outside of the vein. The usual
dose is 30 mg per pound of body weight (15
mL/100 lb). May be repeated at weekly
intervals, if necessary.

WARNING

Not for use in lactating dairy cows.

VETERINARY INDICATIONS

For Animal Use Only

Keep Out of Reach Of Children

CAUTION:

Federal law restricts this drug to use
by or on the order of a licensed veterinarian.

COMPOSITION

Each 100 mL of sterile aqueous solution contains:
Sodium Iodide...................20 grams
Water For Injection.................q.s.

STORAGE AND HANDLING

Store between 15°C-30°C (59°F-86°F).

WARNINGS AND PRECAUTIONS

TAKE TIME OBSERVE LABEL DIRECTIONS

INFORMATION FOR OWNERS/CAREGIVERS

Manufactured by:

Nova-Tech, Inc.

Grand Island, NE 68801 USA

18-819

RMS 92-366

NDC# 65207-819-25

Net Contents:

250 mL (8.45 fl oz)

Assembled in USA

Lot No.

Exp. Date